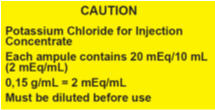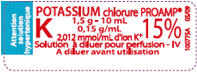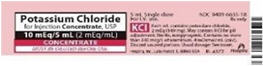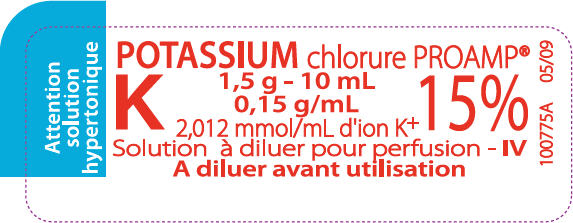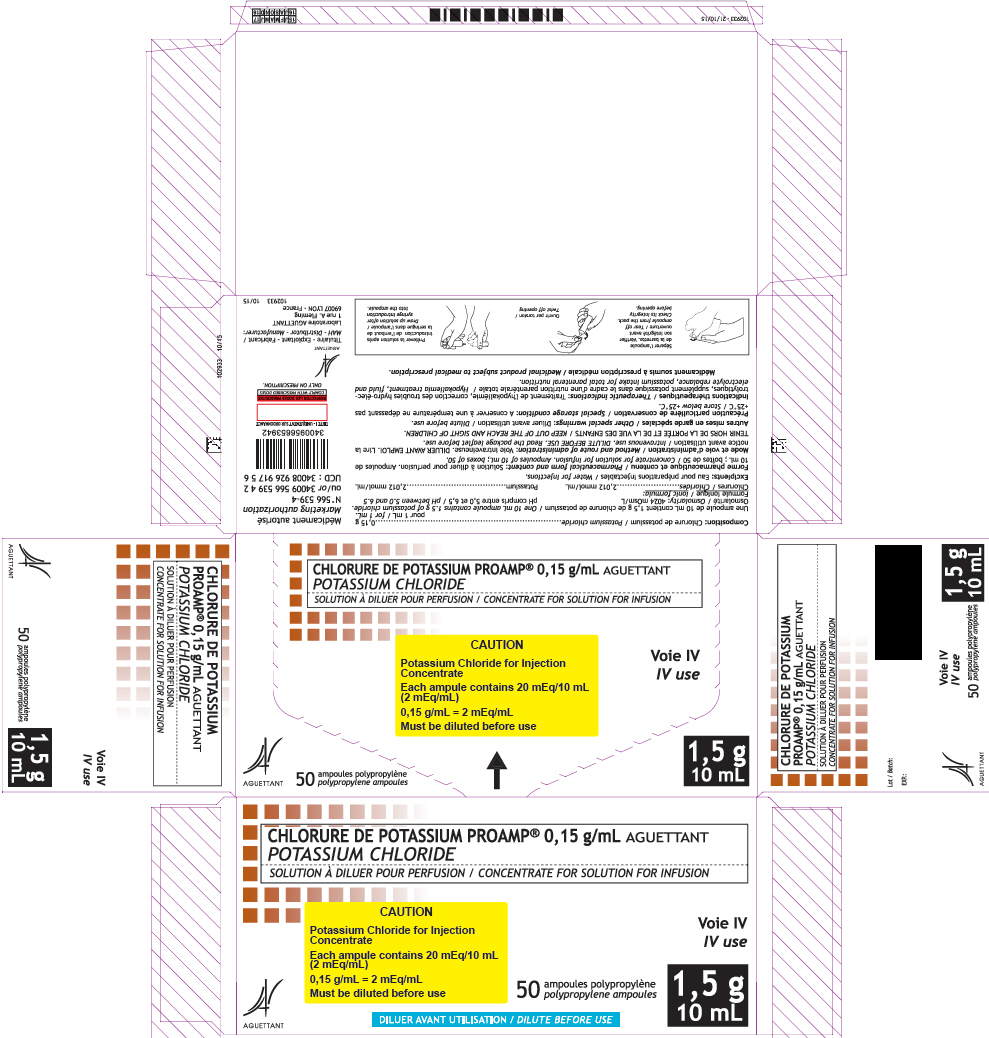 DRUG LABEL: Chlorure de potassium Proamp
NDC: 60710-015 | Form: INJECTION, SOLUTION, CONCENTRATE
Manufacturer: Laboratoire Aguettant
Category: prescription | Type: HUMAN PRESCRIPTION DRUG LABEL
Date: 20180813

ACTIVE INGREDIENTS: potassium chloride 0.15 g/1 mL
INACTIVE INGREDIENTS: WATER

Potassium Chloride for Injection Concentrate, USP

HEALTH CARE PROVIDER LETTER

La Jolla
Pharmaceutical

AGUETTANT
ESSENTIAL
MEDICINES

Important Prescribing Information

Subject: Temporary importation of Potassium Chloride Proamp® 0.15 g/mL (equivalent to 2 mEq/mL), concentrate for solution for infusion to address drug shortage

June, 2018

Dear Healthcare Professional,

Due to the critical shortage of Potassium Chloride for Injection Concentrate 2 mEq/mL, USP in the United States (U.S.) market, Laboratoire Aguettant (Aguettant) is coordinating with the U.S. Food and Drug Administration (FDA) to increase the availability of Potassium Chloride for Injection. Aguettant has initiated temporary importation of its Potassium Chloride Proamp® 0.15 g/mL (equivalent to 2 mEq/mL) concentrate for solution for infusion. This product is manufactured and marketed in France by Aguettant.

Given the scale of this shortage, FDA is coordinating with several firms to import Potassium Chloride for Injection 2 mEq/mL. At this time, however, no other entity except La Jolla Pharmaceutical Company is authorized by the FDA to import or distribute Aguettant's Potassium Chloride Proamp® 0.15 g/mL (equivalent to 2 mEq/mL) concentrate for solution for infusion. FDA has not approved Aguettant's Potassium Chloride Proamp® 0.15 g/mL concentrate for solution for infusion, but allows its temporary importation into the United States. You may be provided with additional letters for other imported products you receive. Please read each letter in its entirety because each letter may contain different, product-specific information.

Effective immediately, and during this temporary period, Aguettant will offer the following presentation of Potassium Chloride for Injection:

Product name and description | Size | Pack factor | NDC Number
Potassium Chloride Proamp® 0.15 g/mL, concentrate for solution for infusion (equivalent to 2 mEq/mL) | 10 mL | 50 ampules per box | 60710-015-50

There are key differences between the labeling of the FDA approved Potassium Chloride for Injection 2 mEq/mL products and Aguettant's imported Potassium Chloride Proamp® 0.15 g/mL.

It is important to note the following:

- Aguettant's product is labeled Potassium Chloride Proamp® 0,15 g/mL which means 0.15 g/mL in the U.S. and is equal to 2 mEq/mL of potassium chloride. We have affixed the following sticker with this information on the carton for the imported product.
- The ampule label of Aguettant's product is in French without English translation. However, the carton and the prescribing information for Aguettant's product is translated into English. Institutions should develop a strategy, which may include labeling the ampules with key information, to ensure safe use of the product.
- Aguettant's product does not contain a barcode. Institutions should manually input the product into their systems. Alternative procedures should be followed to assure that the correct drug product is being used and administered to individual patients.
- Inspect the solution visually for particulate matter and discoloration prior to administration.
- The imported product is packaged in polypropylene 10 mL ampules. To use the ampule, hold it upright, twist off the cap, and withdraw the solution using a syringe.

A side by side comparison of the key differences in the labeling between the FDA-approved product and the imported product is displayed in the product comparison table at the end of this letter.

Please refer to the package insert for the FDA-approved Potassium Chloride for Injection Concentrate, USP drug product for full prescribing information.

To order or if you have questions about Aguettant's Potassium Chloride Proamp® 0.15 g/mL ampules, please contact La Jolla Pharmaceutical Company at 1-800-651-3861.

To report an adverse event concerning the imported Potassium Chloride Proamp® 0.15 g/mL ampules, please contact La Jolla Pharmaceutical Company at 1-800-651-3861. Adverse events or quality problems experienced with the use of the Potassium Chloride Proamp® 0.15 g/mL ampules may also be reported to the FDA's MedWatch Adverse Event Reporting program either online, by regular mail or by fax:

- Complete and submit the report Online: www.fda.gov/medwatch/report.htm
- Regular mail or Fax: Download form www.fda.gov/MedWatch/getforms.htm or call 1-800-332-1088 to request a reporting form, then complete and return to the address on the pre-addressed form, or submit by fax to 1-800-FDA-0178.

If you have any questions about the information contained in this letter or use of Aguettant's Potassium Chloride Proamp® 0.15 g/mL ampules, please contact La Jolla's Medical Information Contact Center (MICC) at 1-800-651-3861.

Sincerely,

Jérôme JOLY
Laboratoire Aguettant
Director, Global QP

Cécile BAILLY
Laboratoire Aguettant
Medical Director

George F. Tidmarsh, MD, PhD
Chief Executive Officer
La Jolla Pharmaceutical Company

Doranne Frano
Vice President, Regulatory Affairs
La Jolla Pharmaceutical Company

PRODUCT COMPARISON TABLE

 | Import Product | U.S. Marketed Product
 | AGUETTANT | HOSPIRA
Presentation
Drug Name | Potassium chloride Proamp® 0.15 g/mL, concentrate for solution for infusion | Potassium Chloride for Injection Concentrate, USP
Active Ingredient Concentration | Potassium: 2.012 mmol/mL Equivalent to: (2 mEq K+/mL) (149 mg/mL) | Each mL contains potassium chloride, 2 mEq (149 mg)
Unit Volume / Volume | 10 ml polypropylene ampules The ampules are made by polypropylene compliant to the 3.1.6. European pharmacopoeia monograph. They are formed through blow fill seal process and are terminally sterilized at 121°C, assuring a maximal level of sterility of the contained solution. | 5 mL single dose vials Semi-rigid plastic vials fabricated from a specially formulated polyolefin.
Indication and Usage | Concentrate for solution for infusion administered to patients suffering from low potassium blood levels (hypokalemia). Potassium is naturally present in body fluids and is needed for normal body function. It can also be used as a potassium supply for patients who are unable to be fed orally and receive total parenteral nutrition. | Potassium Chloride for Injection Concentrate, USP is indicated in the treatment of potassium deficiency states when oral replacement is not feasible.

PRINCIPAL DISPLAY PANEL - 10 mL Ampule Label

POTASSIUM chlorure PROAMP®
1,5 g - 10 mL
0,15 g/mL
2,012 mmol/mL d'ion K^+
Solution à diluer pour perfusion - IV
A diluer avant utilisation

K

15%

PRINCIPAL DISPLAY PANEL - 10 mL Ampule Box

CHLORURE DE POTASSIUM PROAMP® 0, 15 g/mL AGUETTANT
POTASSIUM CHLORIDE

CAUTION

Potassium Chloride for Injection
Concentrate

Each ampule contains 20 mEq/10 mL
(2 mEq/mL)

0,15 g/mL = 2 mEq/mL

Must be diluted before use

IV use

AGUETTANT

50
polypropylene ampoules

1,5 g
10 mL